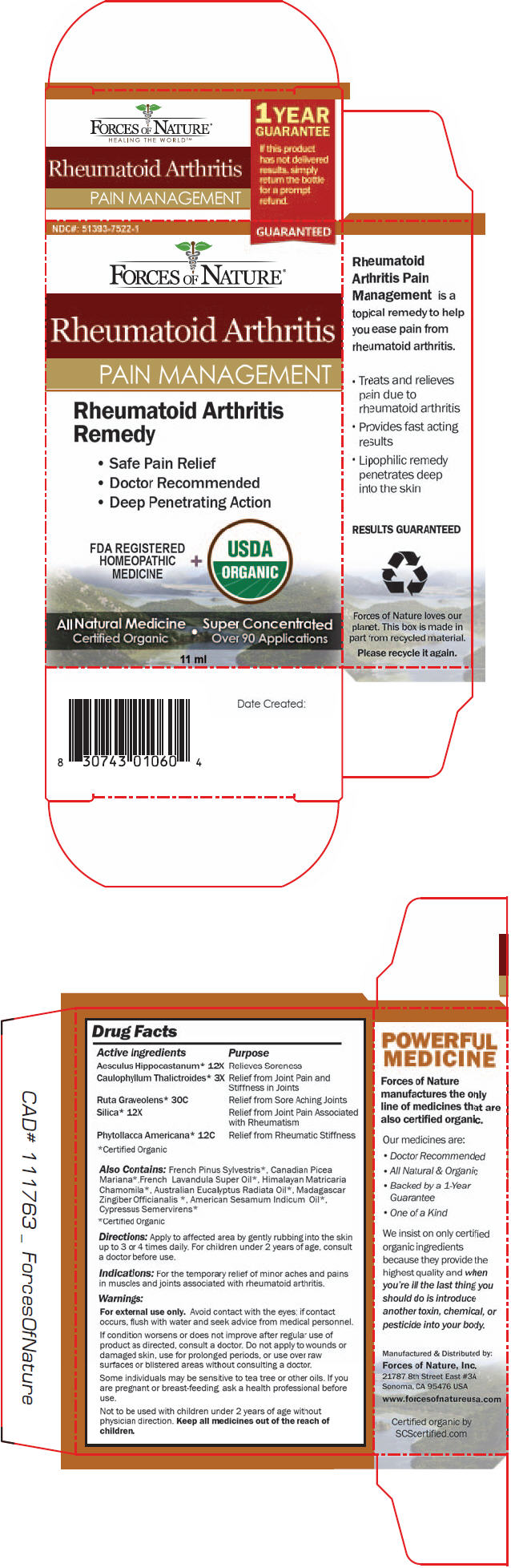 DRUG LABEL: Rheumatoid Arthritis Pain Management
NDC: 51393-7522 | Form: SOLUTION/ DROPS
Manufacturer: Forces of Nature
Category: homeopathic | Type: HUMAN OTC DRUG LABEL
Date: 20131125

ACTIVE INGREDIENTS: Horse Chestnut 12 [hp_C]/100 mL; Caulophyllum Thalictroides Root 3 [hp_X]/100 mL; Phytolacca Americana Root 12 [hp_C]/100 mL; Ruta Graveolens Flowering Top 30 [hp_C]/100 mL; Silicon Dioxide 12 [hp_X]/100 mL
INACTIVE INGREDIENTS: Pine Needle Oil (PINUS SYLVESTRIS); Picea Mariana Leaf Oil; Lavandin Oil; Matricaria Chamomilla Flowering Top Oil; Eucalyptus Radiata Leaf Oil; Ginger; Sesame Oil; Cupressus Sempervirens Whole

Rheumatoid Arthritis Pain Management

Drug Facts

ACTIVE INGREDIENT

Active Ingredient | Purpose
Aesculus Hippocastanum [Certified Organic] 12X, | Relieves Soreness
Caulophyllum Thalictroides 3X | Relief from Joint Pain and Stiffness in Joints
Ruta Graveolens 30C | Relief from Sore Aching Joints
Silica 12X | Relief from Joint Pain Associated with Rheumatism
Phytollacca Americana 12C | Relief from Rheumatic Stiffness

Also Contains

French Pinus Vulgaris [Certified Organic] , Canadian Picea Mariana, French Lavandula Super Oil, Himalayan Matricaria Chamomila, Australian Eucalyptus Radiata Oil, Madagascar Zingiber Officianalis , American Sesamum Indicum Oil

Indications

For the temporary relief of minor aches and pains in muscles and joints associated with rheumatoid arthritis

Directions

Apply to affected area by gently rubbing into the skin up to 3 or 4 times daily. For children under2 years of age, consult a doctor before use.

Warnings

WHEN USING

For external use only. Avoid contact with the eyes; if contact occurs, flush with water and seek advice from medical personnel.

STOP USE

If condition worsens or does not improve after regular use of product as directed, consult a doctor. Do not apply to wounds or damaged skin, use for prolonged periods, or use over raw surfaces or blistered areas without consulting a doctor.

PREGNANCY OR BREAST FEEDING

Some individuals may be sensitive to tea tree or other oils. If you are pregnant or breast-feeding, ask a health professional before use.

KEEP OUT OF REACH OF CHILDREN

Not to be used with children under 2 years of age without physician direction. Keep all medicines out of the reach of children.

Manufactured & Distributed by:
Forces of Nature, Inc.
21787 8th Street East #3A
Sonoma, CA 95476 USA

PRINCIPAL DISPLAY PANEL - 11 ml Bottle Box

NDC#: 51393-7522-1
GUARANTEED

FORCES OF NATURE®

Rheumatoid Arthritis

PAIN MANAGEMENT

Rheumatoid Arthritis
Remedy

- Safe Pain Relief
- Doctor Recommended
- Deep Penetrating Action

FDA REGISTERED
HOMEOPATHIC
MEDICINE
+
USDA
ORGANIC

All Natural Medicine
Certified Organic
•
Super Concentrated
Over 90 Applications

11 ml